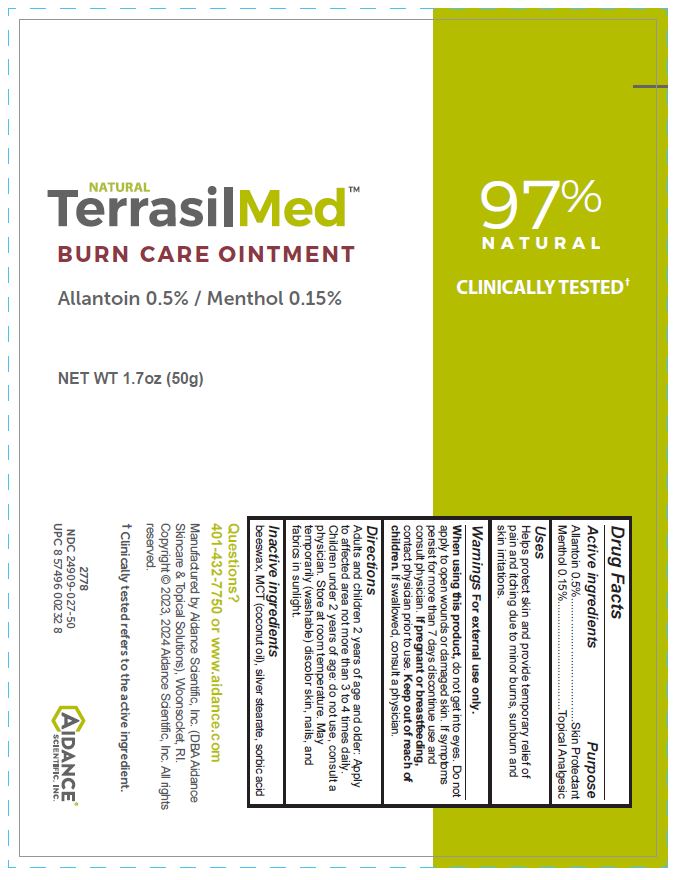 DRUG LABEL: TerrasilMed BURN CARE
NDC: 24909-027 | Form: OINTMENT
Manufacturer: Aidance Scientific, Inc., DBA Aidance Skincare & Topical Solutions
Category: otc | Type: HUMAN OTC DRUG LABEL
Date: 20241125

ACTIVE INGREDIENTS: ALLANTOIN 0.5 g/100 g; MENTHOL 0.15 g/100 g
INACTIVE INGREDIENTS: YELLOW WAX; COCONUT OIL; SILVER STEARATE; SORBIC ACID

24909-027 TerrasilMed BURN CARE

Active ingredients

Allantoin 0.5%, Menthol 0.15%

Purpose

Allantoin 0.5% - Skin Protectant

Menthol 0.15% - Topical Analgesic

Uses

Helps protect skin and provide temporary relief of pain and itching due to minor burns, sunburn, and skin irritations.

Warnings

For external use only.

When using this product, do not get into eyes. Do not apply to open wounds or damaged skin. If symptoms persist for more than 7 days discontinue use and consult physician.

Keep out of reach of children.

OTHER SAFETY INFORMATION

If swallowed, consult a physician.

PREGNANCY OR BREAST FEEDING

If pregnant or breast-feeding contact physician prior to use.

Directions

Adults and children 2 years of age and older: Apply to affected area not more than 3 to 4 times daily. Children under 2 years of age: do not use, consult a physician. Store at room temperature. May temporarily (washable) discolor skin, nails, and fabrics in sunlight.

Inactive ingredients

beeswax, MCT (coconut oil), silver stearate, sorbic acid

Questions?

401-432-7750 or www.aidance.com